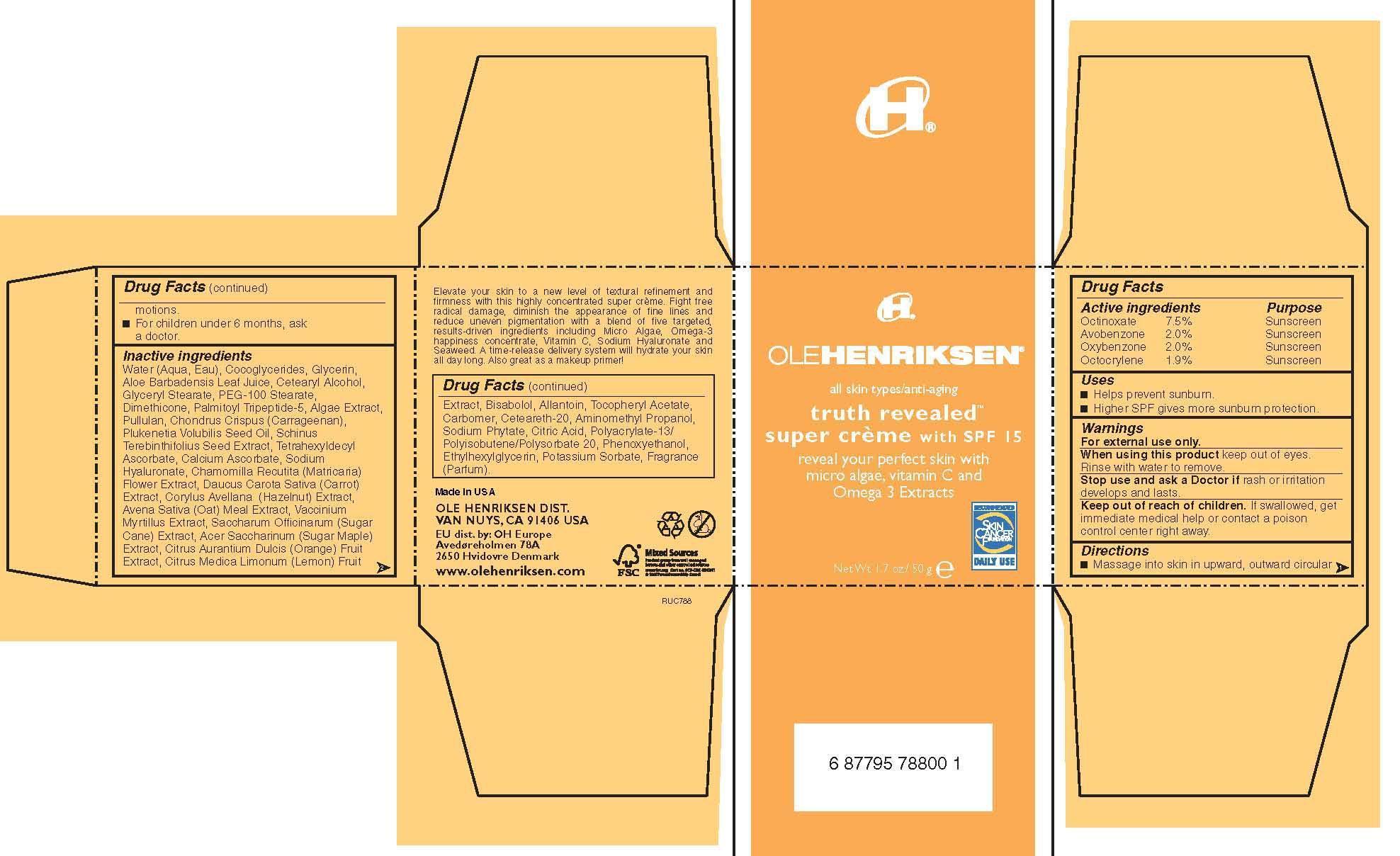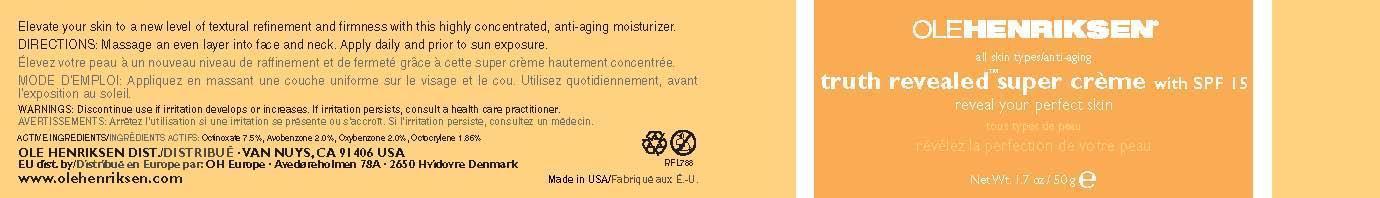 DRUG LABEL: Truth Revealed super creme SPF 15
NDC: 51770-001 | Form: CREAM
Manufacturer: Ole Henriksen
Category: otc | Type: HUMAN OTC DRUG LABEL
Date: 20130708

ACTIVE INGREDIENTS: OCTINOXATE 7.5 g/100 g; AVOBENZONE 2 g/100 g; OXYBENZONE 2 g/100 g; OCTOCRYLENE 1.9 g/100 g
INACTIVE INGREDIENTS: WATER; GLYCERIN; ALOE VERA LEAF; CETOSTEARYL ALCOHOL; GLYCERYL MONOSTEARATE; PEG-100 STEARATE; DIMETHICONE; PALMITOYL TRIPEPTIDE-5; PULLULAN; CHONDRUS CRISPUS; PLUKENETIA VOLUBILIS SEED OIL; TETRAHEXYLDECYL ASCORBATE; CALCIUM ASCORBATE; CHAMOMILE; CARROT; AVENA SATIVA LEAF; VACCINIUM MYRTILLUS LEAF; SUCROSE; ACER SACCHARUM BARK/SAP; ORANGE; LEMON; LEVOMENOL; ALLANTOIN; ALPHA-TOCOPHEROL ACETATE; CARBOMER 934; POLYOXYL 20 CETOSTEARYL ETHER; AMINOMETHYLPROPANOL; PHYTIC ACID; CITRIC ACID MONOHYDRATE; PHENOXYETHANOL; ETHYLHEXYLGLYCERIN; POTASSIUM SORBATE

Truth Revealed Super Creme with SPF 15

Active Ingredient Purpose

Octinoxate 7.5% Sunscreen
Avobenzone 2.0% Sunscreen
Oxybenzone 2.0% Sunscreen
Octocrylene 1.9% Sunscreen

Uses:

Helps prevent sunburn.

Higher SPF gives more sunburn protection.

Keep out of reach of children

Stop use and ask a doctor if rash or irritation develops and lasts

Warnings

For external use only

When using this product keep out of eyes. Rinse with water to remove.

If swallowed, get immediate medical help or contact a poison control center right away.

Directions

Massage into skin in upward motion, outward circular motions

For children under 6 months, ask a doctor.

Inactive Ingredients

Water (Aqua,Eau), cocoglycerides, Glycerin, Aloe Barbadensis Leaf Juice, Cetearyl Alcohol, Glyceryl Stearate, PEG-100 Stearate, Dimethicone, Palmitoyl Tripeptide-5, Algae Extract, Pullulan, Chondrus Chrispus (Carrageenan), Plukenetia Volubilis Seed Oil, Schinus Terebinthifolius Seed Extract, Tetrahexyldecyl Ascorbate, calcium Ascorbate, Sodium Hyaluronate, Chamomilla Recutita (Matricaria) Flower Extract, Daucus Carota Sativa (Carrot) Extract, Corylus Avellana (Hazelnut) extract, Avena Sativa (Oat) Meal Extract. Vaccinum Myrtillus Extract, Saccharum Officinarum (Sugar Cane) Extract, Acer Saccharinum (Sugar Maple) Extract, Citrus Aurantium Dulcis (Orange) Fruit Extract, Citrus Medica Limonium (Lemon) Fruit Extract, Bisabolol, Allantoin, Tocopheryl Acetate, Carbomer, Ceteareth-20, Aminomethyl Propanol, sodium Phytate, Citric Acid, Polyacrylate-13/polyisobutene/polysorbate 20, Phenoxy ethanol, Ethylhexylglycerin, Potassium Sorbate, Fragrance (Parfum)

PACKAGE LABEL

Ole Henriksen

All skin types/anti-aging

Truth Revealed Super Creme with SPF 15

Net. Wt. 1.7 oz/ 50g